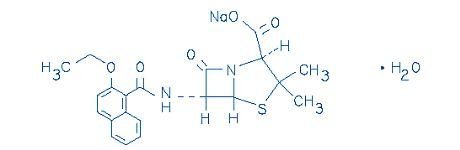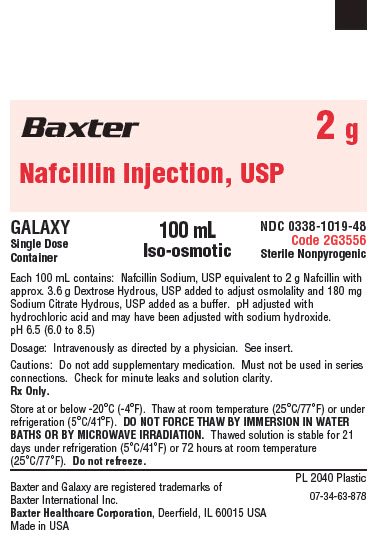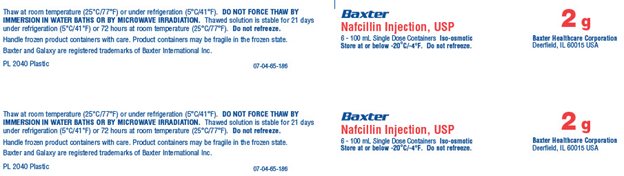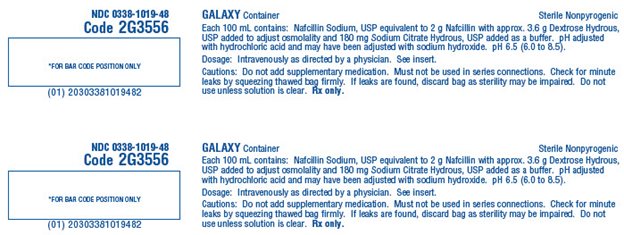 DRUG LABEL: NAFCILLIN
NDC: 0338-1019 | Form: INJECTION, SOLUTION
Manufacturer: Baxter Healthcare Corporation
Category: prescription | Type: HUMAN PRESCRIPTION DRUG LABEL
Date: 20241206

ACTIVE INGREDIENTS: NAFCILLIN SODIUM 2 g/100 mL
INACTIVE INGREDIENTS: DEXTROSE MONOHYDRATE 3.6 g/100 mL; TRISODIUM CITRATE DIHYDRATE 180 mg/100 mL; HYDROCHLORIC ACID; SODIUM HYDROXIDE; WATER

Nafcillin Injection, USP
in Plastic Container
For Intravenous Use Only
GALAXY Container

To reduce the development of drug-resistant bacteria and maintain the effectiveness of Nafcillin Injection, USP and other antibacterial drugs, Nafcillin Injection, USP should be used only to treat or prevent infections that are proven or strongly suspected to be caused by bacteria.

DESCRIPTION

Nafcillin Injection, USP is a sterile injectable product containing nafcillin which is added as Nafcillin Sodium, USP, a semisynthetic penicillin derived from the penicillin nucleus, 6-aminopenicillanic acid. The chemical name of nafcillin sodium is Monosodium (2S,5R,6R)-6-(2-ethoxy-1-naphthamido)-3,3-dimethyl-7-oxo-4-thia-1- azabicyclo[3.2.0]heptane-2-carboxylate monohydrate. It is resistant to inactivation by the enzyme penicillinase (beta-lactamase). The molecular formula of Nafcillin Sodium, USP is C21H21N2NaO5S·H2O. The molecular weight is 454.48. The structural formula of nafcillin sodium is as follows:

Nafcillin Injection, USP is a frozen, iso-osmotic, sterile, nonpyrogenic premixed 100 mL solution containing 2 g of nafcillin, added as Nafcillin Sodium, USP. Dextrose, USP has been added to the above dosages to adjust osmolality (approximately 3.6 g as dextrose hydrous to the 2 g dosage. Sodium Citrate Hydrous, USP has been added as a buffer (approximately 180 mg to the 2 g dosage. The pH has been adjusted with hydrochloric acid and may have been adjusted with sodium hydroxide. The pH is 6.5 (6.0 to 8.5). The solution is intended for intravenous use after thawing to room temperature.

This Galaxy container is fabricated from a specially designed multilayer plastic. Solutions are in contact with the polyethylene layer of this container and can leach out certain chemical components of the plastic in very small amounts within the expiration period. The suitability of the plastic has been confirmed in tests in animals according to the USP biological tests for plastic containers, as well as by tissue culture toxicity studies.

CLINICAL PHARMACOLOGY

In a study of five healthy adults administered a single 500 mg dose of nafcillin by intravenous injection over seven minutes, the mean plasma concentration of the drug was approximately 30 mcg/mL at 5 minutes after injection. The mean area under the plasma concentration-versus-time curve (AUC) for nafcillin in this study was 18.06 mcg·h/mL.

The serum half-life of nafcillin administered by the intravenous route ranged from 33 to 61 minutes as measured in three separate studies.

In contrast to the other penicillinase-resistant penicillins, only about 30% of nafcillin is excreted as unchanged drug in the urine of normal volunteers, and most within the first six hours. Nafcillin is primarily eliminated by nonrenal routes, namely hepatic inactivation and excretion in the bile.

Nafcillin binds to serum proteins, mainly albumin. The degree of protein binding reported for nafcillin is 89.9 ± 1.5%. Reported values vary with the method of study and the investigator.

The concurrent administration of probenecid with nafcillin increases and prolongs plasma concentrations of nafcillin. Probenecid significantly reduces the total body clearance of nafcillin with renal clearance being decreased to a greater extent than nonrenal clearance.

The penicillinase-resistant penicillins are widely distributed in various body fluids, including bile, pleural, amniotic and synovial fluids. With normal doses insignificant concentrations are found in the aqueous humor of the eye. High nafcillin CSF levels have been obtained in the presence of inflamed meninges.

Renal failure does not appreciably affect the serum half-life of nafcillin; therefore, no modification of the usual nafcillin dosage is necessary in renal failure with or without hemodialysis. Hemodialysis does not accelerate the rate of clearance of nafcillin from the blood.

A study which assessed the effects of cirrhosis and extrahepatic biliary obstruction in man demonstrated that the plasma clearance of nafcillin was significantly decreased in patients with hepatic dysfunction. In these patients with cirrhosis and extrahepatic obstruction, nafcillin excretion in the urine was significantly increased from about 30 to 50% of the administered dose, suggesting that renal disease superimposed on hepatic disease could further decrease nafcillin clearance.

Microbiology

Penicillinase-resistant penicillins exert a bactericidal action against penicillin-susceptible microorganisms during the state of active multiplication. All penicillins inhibit the biosynthesis of the bacterial cell wall. Nafcillin sodium has been shown to be active against most isolates of the following microorganism, both in vitro and in clinical infections as described in the INDICATIONS AND USAGE section.

Gram-Positive Bacteria

Staphylococcus aureus (Methicillin-susceptible isolates only)

Susceptibility Test Methods

For specific information regarding susceptibility test interpretive criteria and associated test methods and quality control standards recognized by FDA for this drug, please see: http://www.fda.gov/STIC.

INDICATIONS AND USAGE

Nafcillin is indicated in the treatment of infections caused by penicillinase-producing staphylococci which have demonstrated susceptibility to the drug. Culture and susceptibility tests should be performed initially to determine the causative organism and its susceptibility to the drug (see CLINICAL PHARMACOLOGY - Susceptibility Test Methods).

Nafcillin should not be used in infections caused by organisms susceptible to penicillin G. If the susceptibility tests indicate that the infection is due to methicillin-resistant Staphylococcus species, therapy with Nafcillin Injection, USP should be discontinued and alternative therapy provided.

To reduce the development of drug-resistant bacteria and maintain the effectiveness of Nafcillin Injection, USP and other antibacterial drugs, Nafcillin Injection, USP should be used only to treat or prevent infections that are proven or strongly suspected to be caused by susceptible bacteria. When culture and susceptibility information are available, they should be considered in selecting or modifying antibacterial therapy. In the absence of such data, local epidemiology and susceptibility patterns may contribute to the empiric selection of therapy.

CONTRAINDICATION

A history of a hypersensitivity (anaphylactic) reaction to any penicillin is a contraindication.

Solutions containing dextrose may be contraindicated in patients with known allergy to corn or corn products.

WARNINGS

Serious and occasionally fatal hypersensitivity (anaphylactic) reactions have been reported in patients receiving beta-lactam antibacterial drugs. These reactions are more likely to occur in individuals with a history of penicillin hypersensitivity and/or a history of sensitivity to multiple allergens. Before initiating therapy with Nafcillin, inquire about previous hypersensitivity reactions to penicillins, cephalosporins, or other allergens. If an allergic reaction occurs, discontinue Nafcillin and institute appropriate therapy.

Clostridium difficile associated diarrhea (CDAD) has been reported with use of nearly all antibacterial agents, including Nafcillin Injection, USP, and may range in severity from mild diarrhea to fatal colitis. Treatment with antibacterial agents alters the normal flora of the colon leading to overgrowth of C. difficile.

C. difficile produces toxins A and B which contribute to the development of CDAD. Hypertoxin producing strains of C. difficile cause increased morbidity and mortality, as these infections can be refractory to antimicrobial therapy and may require colectomy. CDAD must be considered in all patients who present with diarrhea following antibiotic use. Careful medical history is necessary since CDAD has been reported to occur over two months after the administration of antibacterial agents.

If CDAD is suspected or confirmed, ongoing antibiotic use not directed against C. difficile may need to be discontinued. Appropriate fluid and electrolyte management, protein supplementation, antibiotic treatment of C. difficile, and surgical evaluation should be instituted as clinically indicated.

PRECAUTIONS

General

Nafcillin should generally not be administered to patients with a history of sensitivity to any penicillin.

Penicillin should be used with caution in individuals with histories of significant allergies and/or asthma. Whenever allergic reactions occur, penicillin should be withdrawn unless, in the opinion of the physician, the condition being treated is life-threatening and amenable only to penicillin therapy. The use of antibiotics may result in overgrowth of nonsusceptible organisms. If new infections due to bacteria or fungi occur, the drug should be discontinued and appropriate measures taken.

The liver/biliary tract is the primary route of nafcillin clearance. Caution should be exercised when patients with concomitant hepatic insufficiency and renal dysfunction are treated with nafcillin.

Prescribing Nafcillin Injection, USP in the absence of a proven or strongly suspected bacterial infection or a prophylactic indication is unlikely to provide benefit to the patient and increases the risk of the development of drug-resistant bacteria.

Laboratory Tests

Bacteriologic studies to determine the causative organisms and their susceptibility to the penicillinase-resistant penicillins should be performed (see CLINICAL PHARMACOLOGY - Microbiology). In the treatment of suspected staphylococcal infections, therapy should be changed to another active agent if culture tests fail to demonstrate the presence of staphylococci.

Periodic assessment of organ system function including renal, hepatic, and hematopoietic should be made during prolonged therapy with nafcillin. White blood cell and differential cell counts should be obtained prior to initiation of therapy and periodically during therapy with nafcillin. Urinalysis, serum blood urea nitrogen, and creatinine determinations should be performed at baseline and periodically during therapy with nafcillin. Serum bilirubin, aspartate aminotransferase (AST), alanine aminotransferase (ALT), alkaline phosphatase, and gamma glutamyl transferase should be obtained at baseline and periodically during therapy, especially when using high nafcillin doses. In patients with worsening hepatic function, the risk versus benefit of continued Nafcillin use should be re-evaluated.

Drug Interactions

Tetracycline, a bacteriostatic antibiotic, may antagonize the bactericidal effect of penicillin, and concurrent use of these drugs should be avoided.

Nafcillin in high dosage regimens, i.e., 2 grams every 4 hours, has been reported to decrease the effects of warfarin. When nafcillin and warfarin are used concomitantly, the prothrombin time should be closely monitored and the dose of warfarin adjusted as necessary. This effect may persist for up to 30 days after nafcillin has been discontinued.

Nafcillin when administered concomitantly with cyclosporine has been reported to result in subtherapeutic cyclosporine levels. The nafcillin-cyclosporine interaction was documented in a patient during two separate courses of therapy. When cyclosporine and nafcillin are used concomitantly in organ transplant patients, the cyclosporine levels should be monitored.

Drug/Laboratory Test Interactions

Nafcillin in the urine can cause a false-positive urine reaction for protein when the sulfosalicyclic acid test is used, but not with the dipstick.

Carcinogenesis, Mutagenesis, Impairment of Fertility

No long term animal studies have been conducted with these drugs. Studies on reproduction (nafcillin) in rats and mice reveal no fetal or maternal abnormalities before conception and continuously through weaning (one generation).

Pregnancy

Reproduction studies have been performed in the mouse with oral doses up to 20 times the human dose and orally in the rat at doses up to 40 times the human dose and have revealed no evidence of impaired fertility or harm to the rodent fetus due to nafcillin. There are, however, no adequate or well-controlled studies in pregnant women. Because animal reproduction studies are not always predictive of human response, nafcillin should be used during pregnancy only if clearly needed.

Nursing Mothers

Penicillins are excreted in human milk. Caution should be exercised when penicillins are administered to a nursing woman.

Pediatric Use

The liver/biliary tract is the principal route of nafcillin elimination. Because of immature hepatic and renal function in pediatric patients, nafcillin excretion may be impaired. Safety and effectiveness in pediatric patients have not been established for the use of intravenous nafcillin.

The potential for toxic effects in pediatric patients from chemicals that may leach from the single dose premixed intravenous preparation in plastic containers has not been determined.

Geriatric Use

Clinical studies of Nafcillin Injection, USP did not include sufficient numbers of subjects aged 65 and over to determine whether they respond differently from younger subjects. Other reported clinical experience has not identified differences in responses between the elderly and younger patients. In general, dose selection for an elderly patient should be cautious, usually starting at the low end of the dosing range, reflecting the greater frequency of decreased hepatic, renal, or cardiac function, and of concomitant disease or other drug therapy.

Nafcillin Injection, USP contains 76.6 mg (3.33 mEq) of sodium per gram. At the usual recommended doses, patients would receive between 230 and 460 mg/day (10.0 and 20.0 mEq) of sodium. The geriatric population may respond with a blunted natriuresis to salt loading. This may be clinically important with regard to such diseases as congestive heart failure.

Information for Patients

Patients should be counseled that antibacterial drugs including Nafcillin Injection, USP should only be used to treat bacterial infections. They do not treat viral infections (e.g., the common cold). When Nafcillin Injection, USP is prescribed to treat a bacterial infection, patients should be told that although it is common to feel better early in the course of therapy, the medication should be taken exactly as directed. Skipping doses or not completing the full course of therapy may (1) decrease the effectiveness of the immediate treatment and (2) increase the likelihood that bacteria will develop resistance and will not be treatable by Nafcillin Injection, USP or other antibacterial drugs in the future.

Diarrhea is a common problem caused by antibiotics which usually ends when the antibiotic is discontinued. Sometimes after starting treatment with antibiotics, patients can develop watery and bloody stools (with or without stomach cramps and fever) even as late as two or more months after having taken the last dose of the antibiotic. If this occurs, patients should contact their physician as soon as possible.

ADVERSE REACTIONS

Body as a Whole

The reported incidence of allergic reactions to penicillin ranges from 0.7 to 10 percent (see WARNINGS). Sensitization is usually the result of treatment, but some individuals have had immediate reactions to penicillin when first treated. In such cases, it is thought that the patients may have had prior exposure to the drug via trace amounts present in milk or vaccines. Two types of allergic reactions to penicillins are noted clinically, immediate and delayed.

Immediate reactions usually occur within 20 minutes of administration and range in severity from urticaria and pruritus to angioedema, laryngospasm, bronchospasm, hypotension, vascular collapse, and death. Such immediate anaphylactic reactions are very rare (see WARNINGS) and usually occur after parenteral therapy but have occurred in patients receiving oral therapy. Another type of immediate reaction, an accelerated reaction, may occur between 20 minutes and 48 hours after administration and may include urticaria, pruritus, and fever.

Although laryngeal edema, laryngospasm, and hypotension occasionally occur, fatality is uncommon. Delayed allergic reactions to penicillin therapy usually occur after 48 hours and sometimes as late as 2 to 4 weeks after initiation of therapy. Manifestations of this type of reaction include serum sickness-like symptoms (i.e., fever, malaise, urticaria, myalgia, arthralgia, abdominal pain) and various skin rashes. Nausea, vomiting, diarrhea, stomatitis, black or hairy tongue, and other symptoms of gastrointestinal irritation may occur, especially during oral penicillin therapy.

Local Reactions

Pain, swelling, inflammation, phlebitis, thrombophlebitis, and occasional skin sloughing at the injection site have occurred with intravenous administration of nafcillin (see DOSAGE AND ADMINISTRATION). Severe tissue necrosis with sloughing secondary to subcutaneous extravasation of nafcillin has been reported.

Nervous System Reactions

Neurotoxic reactions similar to those observed with penicillin G could occur with large intravenous or intraventricular doses of nafcillin especially in patients with concomitant hepatic insufficiency and renal dysfunction (see PRECAUTIONS).

Nephrotoxicity

Renal tubular damage and interstitial nephritis have been associated with the administration of nafcillin. Manifestations of nephrotoxicity are hematuria, proteinuria, and acute kidney injury, and may be associated with rash, fever, and eosinophilia. The majority of cases resolve upon discontinuation of nafcillin. Some patients, however, may require dialysis treatment and may develop permanent renal damage.

Hepatic Reactions

Elevation of liver transaminases and/or cholestasis may occur, specifically with administration of high doses of nafcillin.

Gastrointestinal Reactions

Pseudomembranous colitis has been reported with the use of nafcillin. The onset of pseudomembranous colitis symptoms may occur during or after antibiotic treatment (see WARNINGS).

Metabolic Reactions

Agranulocytosis, neutropenia, and bone marrow depression have been associated with the use of nafcillin.

OVERDOSAGE

Neurotoxic reactions similar to those observed with penicillin G may arise with intravenous doses of nafcillin especially in patients with concomitant hepatic insufficiency and renal dysfunction (see PRECAUTIONS).

In the case of overdosage, discontinue nafcillin, treat symptomatically and institute supportive measures as required. Hemodialysis does not increase the rate of clearance of nafcillin from the blood.

DOSAGE AND ADMINISTRATION

Nafcillin Injection, USP supplied as a premixed frozen solution is to be administered as an intravenous infusion. The usual I.V. dosage for adults is 500 mg every 4 hours. For severe infections, 1 g every 4 hours is recommended. Administer slowly over at least 30 to 60 minutes to minimize the risk of vein irritation and extravasation. Bacteriologic studies to determine the causative organisms and their susceptibility to nafcillin should always be performed. Duration of therapy varies with the type and severity of infection as well as the overall condition of the patient; therefore, it should be determined by the clinical and bacteriological response of the patient. In severe staphylococcal infections, therapy with nafcillin should be continued for at least 14 days. The treatment of endocarditis and osteomyelitis may require a longer duration of therapy.

No dosage alterations are necessary for patients with renal dysfunction, including those on hemodialysis. Hemodialysis does not accelerate nafcillin clearance from the blood.

With intravenous administration, particularly in elderly patients, care should be taken because of the possibility of thrombophlebitis.

Parenteral drug products should be inspected visually for particulate matter and discoloration prior to administration whenever solution and container permit.

Do not add supplementary medication to Nafcillin Injection, USP.

Store in a freezer capable of maintaining a temperature of -20°C (-4°F) or less.

DIRECTIONS FOR USE OF GALAXY CONTAINER

Nafcillin Injection, USP in Galaxy container is for intravenous administration using sterile equipment.

Storage

Store in a freezer capable of maintaining a temperature of -20°C/-4°F.

Thawing of Plastic Containers

Thaw frozen container at room temperature (25°C/77°F) or under refrigeration (5°C/41°F). [DO NOT FORCE THAW BY IMMERSION IN WATER BATHS OR BY MICROWAVE IRRADIATION.] Check for minute leaks by squeezing bag firmly. If leaks are detected, discard solution as sterility may be impaired.

Do not add supplementary medication.

Visually inspect the container. If the outlet port protector is damaged, detached, or not present, discard container as solution path sterility may be impaired. Components of the solution may precipitate in the frozen state and will dissolve upon reaching room temperature with little or no agitation. Potency is not affected. Agitate after solution has reached room temperature. If after visual inspection the solution remains cloudy or if an insoluble precipitate is noted or if any seals are not intact, the container should be discarded.

The thawed 2 g solutions are stable for 21 days under refrigeration (5°C/41°F) or 72 hours at room temperature (25°C/77°F). Do not refreeze.

Caution: Do not use plastic containers in series connections. Such use could result in air embolism due to residual air being drawn from the primary container before administration of the fluid from the secondary container is complete.

Preparation for intravenous administration

1. Suspend container from eyelet support.
2. Remove protector from outlet port at bottom of container.
3. Attach administration set. Refer to complete directions accompanying set.

HOW SUPPLIED/STORAGE AND HANDLING

Nafcillin Injection, USP is supplied as a premixed frozen iso-osmotic solution in 100 mL single dose Galaxy containers as follows:

NDC 0338-1019-48 2 grams nafcillin in 100 mL

Store at or below -20°C/-4°F. See Directions for Use of GALAXY Container.

Handle frozen product containers with care. Product containers may be fragile in the frozen state.

Baxter and Galaxy are trademarks of Baxter International Inc. or its subsidiaries.

Baxter Healthcare Corporation
Deerfield, IL 60015 USA
Printed in USA

07-19-08-966
Rev. December 2024

PACKAGE LABELING - PRINCIPAL DISPLAY PANEL

Baxter Logo

2 g

Nafcillin Injection, USP

GALAXY
Single Dose
Container

100 mL
Iso-osmotic

NDC 0338-1019-48
Code 2G3556
Sterile Nonpyrogenic

Each 100 mL contains: Nafcillin Sodium, USP equivalent to 2 g Nafcillin with
approx. 3.6 g Dextrose Hydrous, USP added to adjust osmolality and 180 mg
Sodium Citrate Hydrous, USP added as a buffer. pH adjusted with
hydrochloric acid and may have been adjusted with sodium hydroxide.
pH 6.5 (6.0 to 8.5).

Dosage: Intravenously as directed by a physician. See insert.

Cautions: Do not add supplementary medication. Must not be used in series
connections. Check for minute leaks and solution clarity.
Rx only.

Store at or below -20°C (-4°F). Thaw at room temperature (25°C/77°F) or under
refrigeration (5°C/41°F). DO NOT FORCE THAW BY IMMERSION IN WATER
BATHS OR BY MICROWAVE IRRADIATION. Thawed solution is stable for 21
days under refrigeration (5°C/41°F) or 72 hours at room temperature
(25°C/77°F). Do not refreeze.

Baxter and Galaxy are registered trademarks of
Baxter International Inc.
Baxter Healthcare Corporation
Deerfield, IL 60015 USA
Made in USA

PL 2040 Plastic
07-34-63-878

Baxter Logo
Nafcillin Injection, USP
6 - 100 mL Single Dose Containers Iso-osmotic
Store at or below -20°C/-4°F. Do not refreeze.

2 g
Baxter Healthcare Corporation
Deerfield, IL 60015 USA

Thaw at room temperature (25°C/77°F) or under refrigeration (5°C/41°F). DO NOT FORCE THAW BY IMMERSION IN WATER BATHS OR BY MICROWAVE IRRADIATION. Thawed solution is stable for 21 days under refrigeration (5°C/41°F) or 72 hours at room temperature (25°C/77°F). Do not refreeze.

Handle frozen product containers with care. Product containers may be fragile in the frozen state.

Baxter and Galaxy are registered trademarks of Baxter International Inc.

PL 2040 Plastic
07-04-65-186

NDC 0338-1019-48
Code 2G3556
FOR BAR CODE POSITION ONLY
(01) 20303381019482

GALAXY Container
Sterile Nonpyrogenic
Each 100 mL contains: Nafcillin Sodium, USP equivalent to 2 g Nafcillin with approx. 3.6 g Dextrose Hydrous, USP added to adjust osmolality and 180 mg Sodium Citrate Hydrous, USP added as a buffer. pH adjusted with hydrochloric acid and may have been adjusted with sodium hydroxide. pH 6.5 (6.0 to 8.5).

Dosage: Intravenously as directed by a physician. See insert.

Cautions: Do not add supplementary medication. Must not be used in series connections. Check for minute leaks by squeezing thawed bag firmly. If leaks are found, discard bag as sterility may be impaired. Do not use unless solution is clear. Rx only.